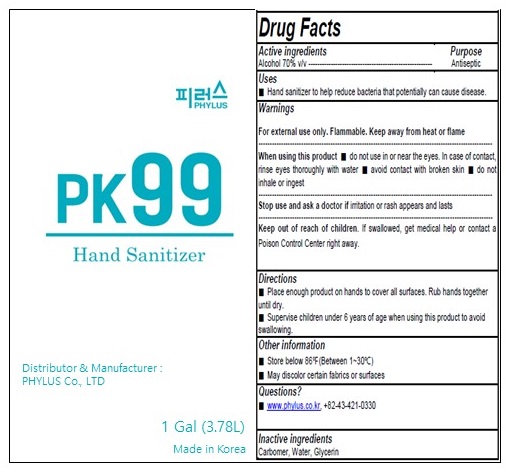 DRUG LABEL: PK 99 Hand Sanitizer
NDC: 77448-030 | Form: GEL
Manufacturer: PHYLUS CO.,LTD
Category: otc | Type: HUMAN OTC DRUG LABEL
Date: 20200727

ACTIVE INGREDIENTS: ALCOHOL 0.7 L/1 L
INACTIVE INGREDIENTS: CARBOMER HOMOPOLYMER, UNSPECIFIED TYPE; WATER; Glycerin

ACTIVE INGREDIENT

Alcohol 70% v/v

INACTIVE INGREDIENT

Carbomer, Water, Glycerin

PURPOSE

Antiseptic

WARNINGS

For external use only. Flammable. Keep away from heat or flame
--------------------------------------------------------------------------------------------------------
When using this product ■ do not use in or near the eyes. In case of contact, rinse eyes thoroughly with water ■ avoid contact with broken skin ■ do not inhale or ingest
--------------------------------------------------------------------------------------------------------
Stop use and ask a doctor if irritation or rash appears and lasts

KEEP OUT OF REACH OF CHILDREN

If swallowed, get medical help or contact a Poison Control Center right away.

Uses

■ Hand sanitizer to help reduce bacteria that potentially can cause disease.

Directions

■ Place enough product on hands to cover all surfaces. Rub hands together until dry.
■ Supervise children under 6 years of age when using this product to avoid swallowing.

Other information

■ Store below 86℉(Between 1~30℃)
■ May discolor certain fabrics or surfaces

Questions?

■ www.phylus.co.kr , +82-43-421-0330